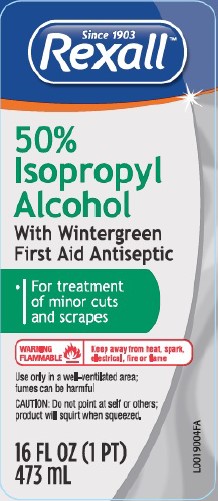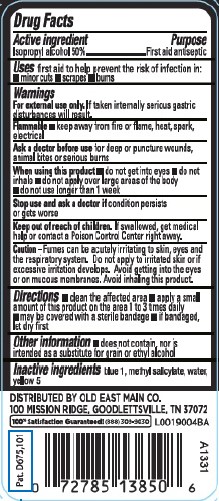 DRUG LABEL: Isopropyl
NDC: 55910-211 | Form: SOLUTION
Manufacturer: Old East Main Co.
Category: otc | Type: HUMAN OTC DRUG LABEL
Date: 20260302

ACTIVE INGREDIENTS: ISOPROPYL ALCOHOL 50 mL/100 mL
INACTIVE INGREDIENTS: FD&C BLUE NO. 1; METHYL SALICYLATE; WATER; FD&C YELLOW NO. 5

Rexall 211.002/211AC-AD
50% Isopropyl Alcohol with Wintergreen

Active ingredient

Isopropyl Alcohol 50%

Purpose

First aid antiseptic

Uses

first aid to help prevent the risk of infection in:

- minor cuts
- scrapes
- burns

Warnings

For external use only.If taken internally serious gastric disturbances will result.

Flammable

- keep away from fire or flame, heat, spark, electrical

Ask a doctor before use

for deep or puncture wounds, animal bites or serious burns

when using this product

- do not get into eyes
- do not inhale
- do not apply over large areas of the body
- do not use longer than 1 week

stop use and ask a doctor if

condition persists or gets worse

Keep out of reach of children

if swallowed, get medical help or contact a Poison Control Center right away

Caution

Fumes can be acutely irritating to skin, eyes and the respiratory system. Do not apply to irritated skin or if excessive irritation develops. Avoid getting into the eyes or on mucous membranes. Avoid inhaling this product.

Directions

- clean the affected area
- apply a small amount of this product on the area 1 to 3 times daily
- may be covered with a sterile bandage
- if bandaged, let dry first

Other information

- does not contain, nor is intended as a substitute for grain or ethyl alcohol

Inactive ingredients

blue 1, methyl salicylate, water, yellow 5

adverse reactions section

DISTRIBUTED BY OLD EAST MAIN CO.

100 MISSION RIDGE, GOODLETTSVILLE, TN 37072

100% Satisfaction Guaranteed! (888)309-9030

Pat. D675, 101

principal display panel

Since 1903

Rexall™

50%

Isopropyl

Alcohol

With Wintergreen

First Aid Antiseptic

- For treatment of minor cuts and scrapes

WARNING FLAMMABLE - Keep away from heat, spark, electrical, fire or flame

Use only in a well-ventilated area; fumes can be harmful

CAUTION: Do not point at self or others; product will squirt when squeezed

16 FL OZ (1 PT) 473 mL